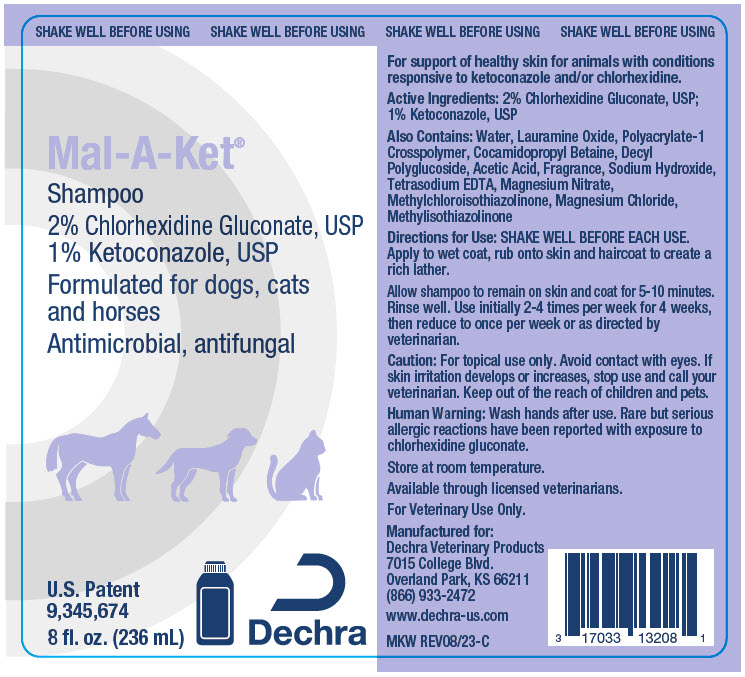 DRUG LABEL: Mal-A-Ket
NDC: 17033-131 | Form: SHAMPOO, SUSPENSION
Manufacturer: Dechra Veterinary Products
Category: animal | Type: OTC ANIMAL DRUG LABEL
Date: 20231212

ACTIVE INGREDIENTS: CHLORHEXIDINE GLUCONATE 20 mg/1 mL; KETOCONAZOLE 10 mg/1 mL

Mal-A-Ket® Shampoo

VETERINARY INDICATIONS

For support of healthy skin for animals with conditions responsive to ketoconazole and/or chlorhexidine.

DESCRIPTION

Active Ingredients: 2% Chlorhexidine Gluconate, USP; 1% Ketoconazole, USP

Also Contains: Water, Lauramine Oxide, Polyacrylate-1 Crosspolymer, Cocamidopropyl Betaine, Decyl Polyglucoside, Acetic Acid, Fragrance, Sodium Hydroxide, Tetrasodium EDTA, Magnesium Nitrate, Methylchloroisothiazolinone, Magnesium Chloride, Methylisothiazolinone

DOSAGE AND ADMINISTRATION

Directions for Use: SHAKE WELL BEFORE EACH USE. Apply to wet coat, rub onto skin and haircoat to create a rich lather. Allow shampoo to remain on skin and coat for 5-10 minutes. Rinse well. Use initially 2-4 times per week for 4 weeks, then reduce to once per week or as directed by veterinarian.

SAFE HANDLING WARNING

Caution: For topical use only. Avoid contact with eyes. If skin irritation develops or increases, stop use and call your veterinarian. Keep out of the reach of children and pets.

WARNINGS

Human Warning: Wash hands after use. Rare but serious allergic reactions have been reported with exposure to chlorhexidine gluconate.

STORAGE AND HANDLING

Store at room temperature.

Available through licensed veterinarians.

For Veterinary Use Only.

Manufactured for:
Dechra Veterinary Products
7015 College Blvd.
Overland Park, KS 66211
(866) 933-2472
www.dechra-us.com

MKW REV08/23-C

PRINCIPAL DISPLAY PANEL - 236 mL Bottle Label

SHAKE WELL BEFORE USING

Mal-A-Ket®

Shampoo
2% Chlorhexidine Gluconate, USP
1% Ketoconazole, USP

Formulated for dogs, cats
and horses

Antimicrobial, antifungal

U.S. Patent
9,345,674

8 fl. oz. (236 mL)

Dechra